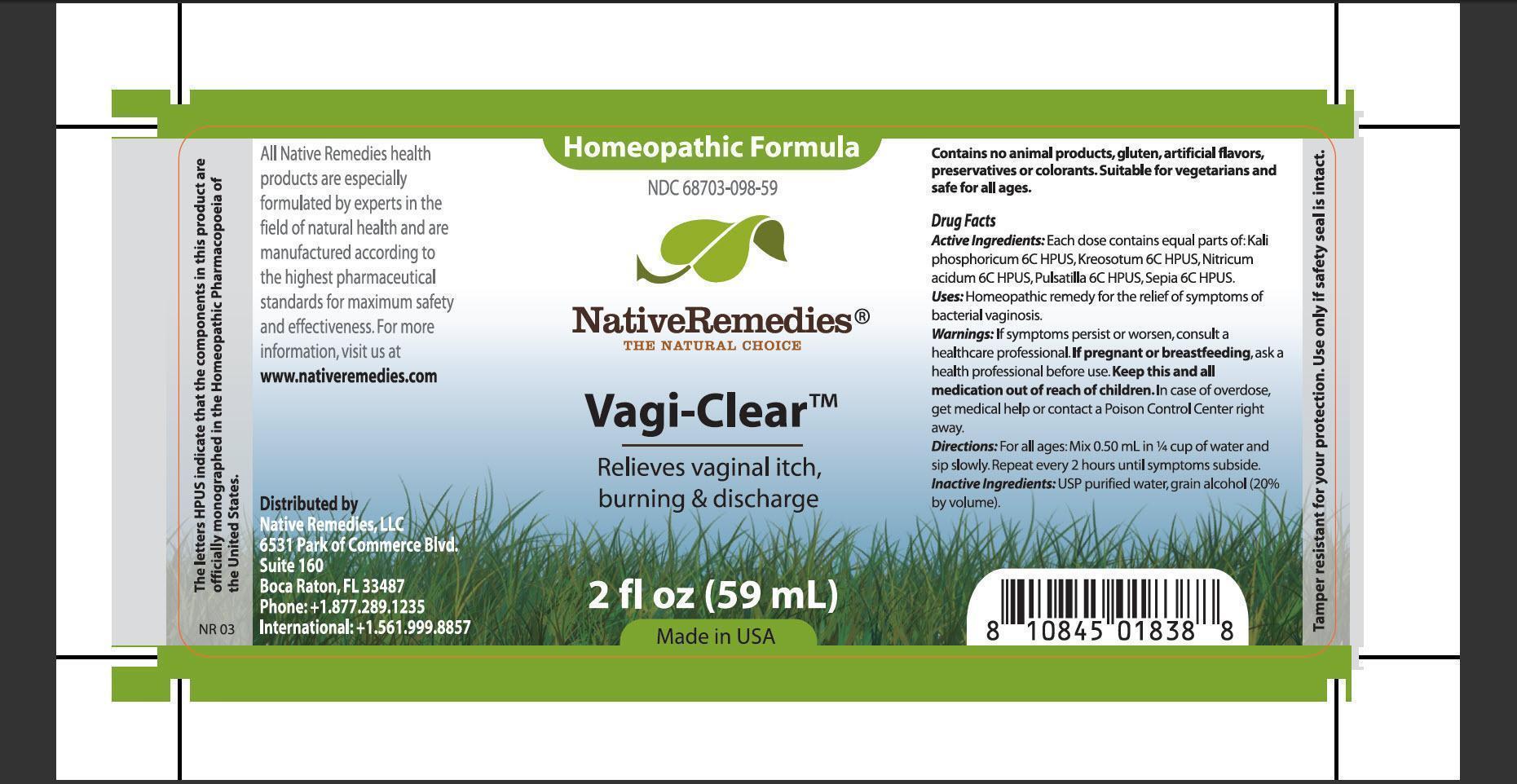 DRUG LABEL: Vagi-Clear
NDC: 68703-098 | Form: TINCTURE
Manufacturer: Native Remedies, 
Category: homeopathic | Type: HUMAN OTC DRUG LABEL
Date: 20130405

ACTIVE INGREDIENTS: POTASSIUM PHOSPHATE, DIBASIC 6 [hp_C]/1 mL; WOOD CREOSOTE 6 [hp_C]/1 mL; NITRIC ACID 6 [hp_C]/1 mL; PULSATILLA VULGARIS 6 [hp_C]/1 mL; SEPIA OFFICINALIS JUICE 6 [hp_C]/1 mL
INACTIVE INGREDIENTS: WATER; ALCOHOL

Vagi-Clear

PURPOSE

Relieves vaginal itch, burning and discharge

ACTIVE INGREDIENT

Active Ingredients: Each dose contains equal parts of: Kali phosphoricum 6C HPUS, Kreosotum 6C HPUS, Nitricum acidum 6C HPUS, Pulsatilla 6C HPUS, Sepia 6C HPUS

INDICATIONS AND USAGE

Uses: Homeopathic remedy for the relief of symptoms of bacterial vaginosis

WARNINGS

Warnings: If symptoms persist or worsen, consult a healthcare professional

PREGNANCY OR BREAST FEEDING

If pregnant or breastfeeding, ask a health professional before use

KEEP OUT OF REACH OF CHILDREN

Keep this and all medication out of reach of children

OVERDOSAGE

In case of overdose, get medical help or contact a Poison Control Center right away

DOSAGE AND ADMINISTRATION

Directions: For all ages: Mix 0.50 mL in 1/4 cup of water and sip slowly. Repeat every two hours until symptoms subside.

INACTIVE INGREDIENT

Inactive Ingredients: USP purified water, grain alcohol (20% by volume)

PATIENT COUNSELING INFORMATION

The letters HPUS indicate that the components in this product are officially monographed in the Homeopathic Pharmacopoeia of the United States

All Native Remedies health products are especially formulated by experts in the field of natural health and are manufactured according to the highest pharmaceutical standards for maximum safety and effectiveness. For more information, visit us at www.nativeremedies.com

Distributed by
Native Remedies, LLC
6531 Park of Commerce Blvd.
Suite 160
Boca Raton, Fl 33487
Phone: +13.877.289.1235
International: +1.561.999.8857

Contains no animal products, gluten, artificial flavors, preservatives or colorants. Suitable for vegetarians and safe for all ages

STORAGE AND HANDLING

Tamper resistant for your protection. Use only if safety seal is intact